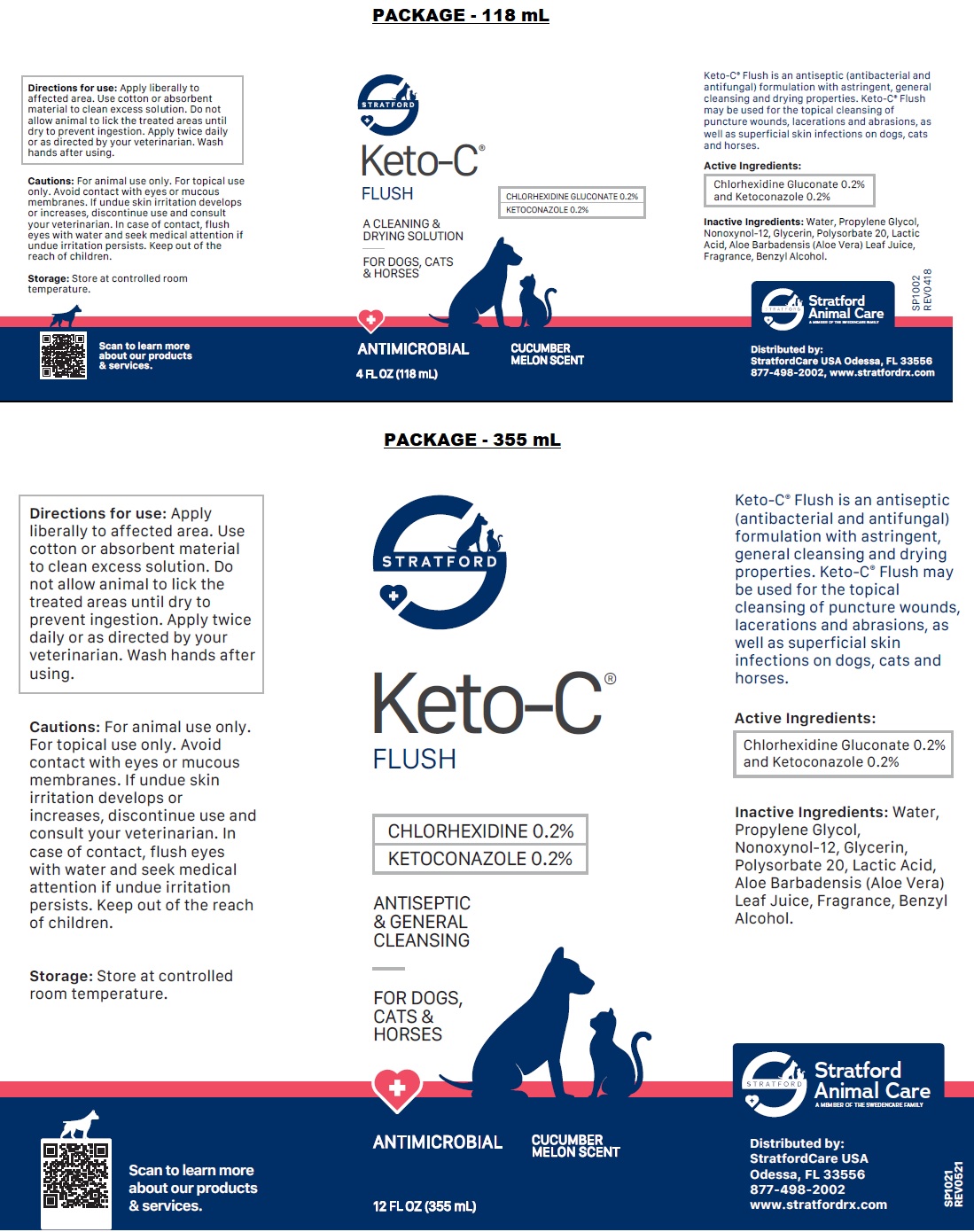 DRUG LABEL: Keto-C FLUSH
NDC: 86069-102 | Form: SOLUTION
Manufacturer: Stratford Care Usa, Inc.
Category: animal | Type: OTC ANIMAL DRUG LABEL
Date: 20221108

ACTIVE INGREDIENTS: CHLORHEXIDINE GLUCONATE 0.2 g/100 mL; KETOCONAZOLE 0.2 g/100 mL
INACTIVE INGREDIENTS: WATER; PROPYLENE GLYCOL; NONOXYNOL-12; GLYCERIN; POLYSORBATE 20; LACTIC ACID, UNSPECIFIED FORM; ALOE VERA LEAF; BENZYL ALCOHOL

Keto-C® FLUSH

Active Ingredients:

Chlorhexidine Gluconate 0.2% and Ketoconazole 0.2%

PURPOSE

antibacterial and antifungal

INDICATIONS AND USAGE

Keto-C® Flush is an antiseptic (antibacterial and antifungal) formulation with astringent, general cleansing and drying properties. Keto-C® Flush may be used for the topical cleansing of puncture wounds, lacerations and abrasions, as well as superficial skin infections on dogs, cats and horses.

INACTIVE INGREDIENT

Inactive Ingredients: Water, Propylene Glycol, Nonoxynol-12, Glycerin, Polysorbate 20, Lactic Acid, Aloe Barbadensis (Aloe Vera) Leaf Juice, Fragrance, Benzyl Alcohol.

DOSAGE AND ADMINISTRATION

Directions for use: Apply liberally to affected area. Use cotton or absorbent material to clean excess solution. Do not allow animal to lick the treated areas until dry to prevent ingestion. Apply twice daily or as directed by your veterinarian. Wash hands after using.

PRECAUTIONS

Cautions: For animal use only. For topical use only. Avoid contact with eyes or mucous membranes. If undue skin irritation develops or increases, discontinue use and consult your veterinarian. In case of contact, flush eyes with water and seek medical attention if undue irritation persists. Keep out of the reach of children.

Storage: Store at controlled room temperature.

ANTISEPTIC & GENERAL CLEANSING

FOR DOGS, CATS & HORSES

ANTIMICROBIAL

CUCUMBER MELON SCENT

Stratford Animal Care
A MEMBER OF THE SWEDENCARE FAMILY

Distributed by:
StratfordCare USA
Odessa, FL 33556
877-498-2002
www.stratfordrx.com